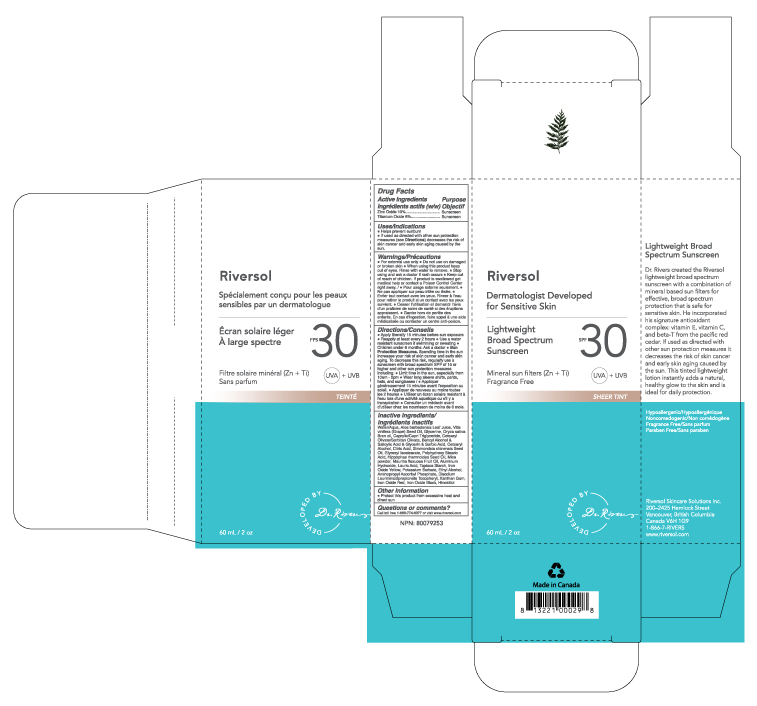 DRUG LABEL: Riversol Lightweight Broad Spectrum Sunscreen Spf 30
NDC: 72019-0001 | Form: CREAM
Manufacturer: Riversol Skincare Solutions Inc
Category: otc | Type: HUMAN OTC DRUG LABEL
Date: 20200120

ACTIVE INGREDIENTS: ZINC OXIDE 100 mg/1 mL; TITANIUM DIOXIDE 0.09883 g/1 mL
INACTIVE INGREDIENTS: WATER; ALOE VERA LEAF; VITIS VINIFERA SEED; GLYCERIN; ORYZA SATIVA WHOLE; BENZYL ALCOHOL; MAURITIA FLEXUOSA FRUIT OIL; ALUMINUM HYDROXIDE; POTASSIUM SORBATE; XANTHAN GUM; LAURIC ACID; STARCH, TAPIOCA; ALCOHOL; AMINOPROPYL ASCORBYL PHOSPHATE; DISODIUM LAURIMINODIPROPIONATE TOCOPHERYL PHOSPHATE; FERRIC OXIDE RED; SORBIC ACID; CAPRYLIC/CAPRIC ACID; SALICYLIC ACID; CITRIC ACID ACETATE; SIMMONDSIA CHINENSIS SEED; GLYCERYL ISOSTEARATE; POLYHYDROXYSTEARIC ACID STEARATE; HIPPOPHAE RHAMNOIDES SEED OIL; MICA; FERRIC OXIDE YELLOW; .BETA.-THUJAPLICIN; CETEARYL OLIVATE; CETOSTEARYL ALCOHOL; FERROSOFERRIC OXIDE

Riversol Lightweight Broad Spectrum Sunscreen Spf 30

Active Ingredients

Zinc Oxide 10%

Titanium Oxide 6%

Uses

Helps Prevent Sunburn

If used as directed with other sun protection measures (see Directions) decreases the risk of skin cancer and early skin aging caused by sun.

Warnings

For external use only

Do not use on damaged or broken skin

When using this product keep out of eyes. Rinse with water to remove.

Stop using and ask a doctor is rash occurs

Keep out of reach of children. If product is swallowed get medical help or contact a Poison Control Centre right away.

Directions

Apply liberally 15 minutes before sun exposure.

Reapply at least every 2 hours.

Use a water resistant sunscreen if swimming or sweating

Childre under 6 months: Ask a doctor

Sun Protection Measures. Spending time in the sun increases you risk of skin cancer and early skin aging. To decrease this risk, regularly use a sunscreen with broad spectrum SPF of 15 or higher and other sun protection measures including: Limit time in the sun, especially from 10am - 2 pm Wear long sleeve shirts, pants, hats and sunglasses.

Other Information

Protect this product from excessive heat and direct sun.

Questions or comments?

Call toll free 1-866-774-8377 or visit www.riversol.com

Principal Display Panel

Riversol

Dermatologist Developed fo Sensitive Skin

Lightweight Broad Spectrum Sunscreen

Mineral sun filters (Zn + Ti)

Fragrance Free

SPF 30

Sheer Tint

60 mL / 2 oz